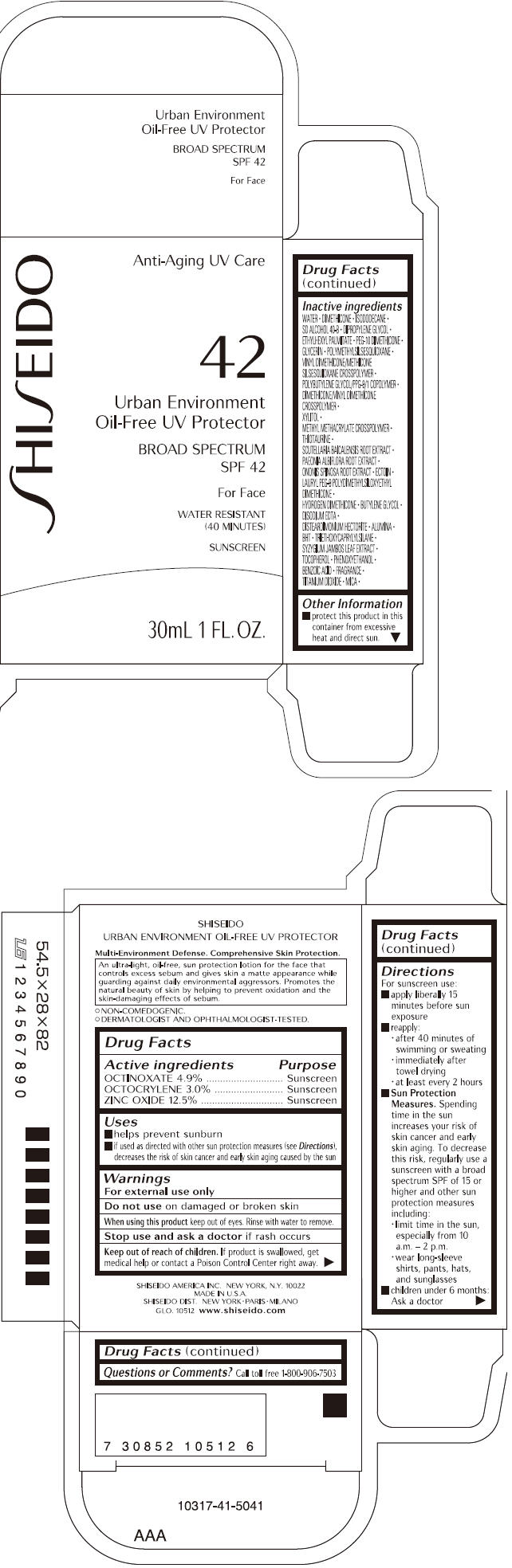 DRUG LABEL: SHISEIDO URBAN ENVIRONMENT 
NDC: 52686-272 | Form: LOTION
Manufacturer: SHISEIDO AMERICA INC.
Category: otc | Type: HUMAN OTC DRUG LABEL
Date: 20191219

ACTIVE INGREDIENTS: OCTINOXATE 1557 mg/31.77 g; OCTOCRYLENE 953 mg/31.77 g; ZINC OXIDE 3971 mg/31.77 g
INACTIVE INGREDIENTS: WATER; DIMETHICONE; ISODODECANE; DIPROPYLENE GLYCOL; ETHYLHEXYL PALMITATE; PEG-10 DIMETHICONE (600 CST); GLYCERIN; POLYMETHYLSILSESQUIOXANE (4.5 MICRONS); XYLITOL; THIOTAURINE; SCUTELLARIA BAICALENSIS ROOT; PAEONIA LACTIFLORA ROOT; ONONIS SPINOSA ROOT; ECTOINE; BUTYLENE GLYCOL; EDETATE DISODIUM; ALUMINUM OXIDE; BUTYLATED HYDROXYTOLUENE; TRIETHOXYCAPRYLYLSILANE; SYZYGIUM JAMBOS LEAF; TOCOPHEROL; PHENOXYETHANOL; BENZOIC ACID; TITANIUM DIOXIDE; MICA

SHISEIDO URBAN ENVIRONMENT OIL-FREE UV PROTECTOR
CREAM

Drug Facts

ACTIVE INGREDIENT

ACTIVE INGREDIENTS: | Purpose
OCTINOXATE 4.9% | Sunscreen
OCTOCRYLENE 3.0% | Sunscreen
ZINC OXIDE 12.5% | Sunscreen

Uses

- helps prevent sunburn
- if used as directed with other sun protection measures (see Directions), decreases the risk of skin cancer and early skin aging caused by the sun

Warnings

For external use only

Do not use on damaged or broken skin

When using this product keep out of eyes. Rinse with water to remove.

Stop use and ask a doctor if rash occurs

Keep out of reach of children. If product is swallowed, get medical help or contact a Poison Control Center right away.

Directions

For sunscreen use:

- apply liberally 15 minutes before sun exposure
- reapply:
  - after 40 minutes of swimming or sweating
  - immediately after towel drying
  - at least every 2 hours
- Sun Protection Measures. Spending time in the sun increases your risk of skin cancer and early skin aging. To decrease this risk, regularly use a sunscreen with a broad spectrum SPF of 15 or higher and other sun protection measures including:
  - limit time in the sun, especially from 10 a.m. – 2 p.m.
  - wear long-sleeve shirts, pants, hats, and sunglasses
- children under 6 months: Ask a doctor

Inactive Ingredients

WATER, DIMETHICONE, ISODODECANE, SD ALCOHOL 40-B, DIPROPYLENE GLYCOL, ETHYLHEXYL PALMITATE, PEG-10 DIMETHICONE, GLYCERIN, POLYMETHYLSILSESQUIOXANE, VINYL DIMETHICONE/METHICONE SILSESQUIOXANE CROSSPOLYMER, POLYBUTYLENE GLYCOL/PPG-9/1 COPOLYMER, DIMETHICONE/VINYL DIMETHICONE CROSSPOLYMER, XYLITOL, METHYL METHACRYLATE CROSSPOLYMER, THIOTAURINE, SCUTELLARIA BAICALENSIS ROOT EXTRACT, PAEONIA ALBIFLORA ROOT EXTRACT, ONONIS SPINOSA ROOT EXTRACT, ECTOIN, LAURYL PEG-9 POLYDIMETHYLSILOXYETHYL DIMETHICONE, HYDROGEN DIMETHICONE, BUTYLENE GLYCOL, DISODIUM EDTA, DISTEARDIMONIUM HECTORITE, ALUMINA, BHT, TRIETHOXYCAPRYLYLSILANE, SYZYGIUM JAMBOS LEAF EXTRACT, TOCOPHEROL, PHENOXYETHANOL, BENZOIC ACID, FRAGRANCE, TITANIUM DIOXIDE, MICA,

Other information

- protect this product in this container from excessive heat and direct sun.

Questions or comments?

Call toll free 1-800-906-7503

SHISEIDO AMERICA INC. NEW YORK, N.Y. 10022
SHISEIDO DIST. NEW YORK • PARIS • MILANO

PRINCIPAL DISPLAY PANEL - 30mL Bottle Carton

SHISEIDO

Anti-Aging UV Care

42

Urban Environment
Oil-Free UV Protector

BROAD SPECTRUM
SPF 42

For Face

WATER RESISTANT
(40 MINUTES)

SUNSCREEN

30mL 1 FL. OZ.